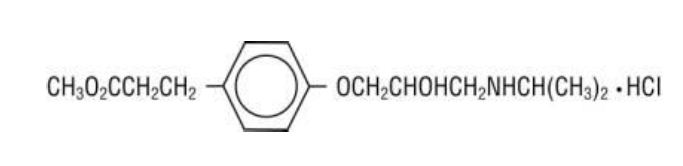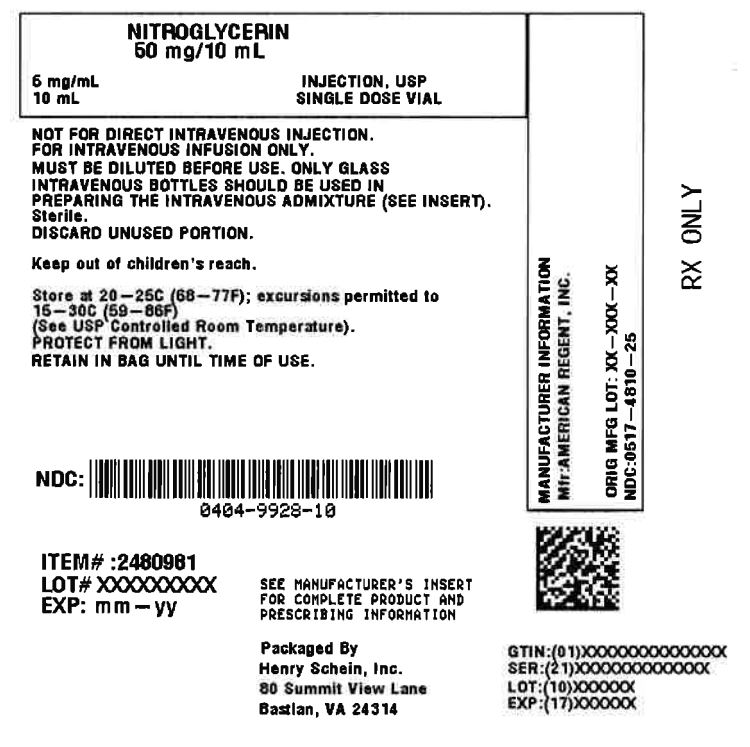 DRUG LABEL: Nitroglycerin
NDC: 0404-9928 | Form: INJECTION, SOLUTION
Manufacturer: Henry Schein, Inc.
Category: prescription | Type: HUMAN PRESCRIPTION DRUG LABEL
Date: 20251106

ACTIVE INGREDIENTS: Nitroglycerin 5 mg/1 mL

Nitroglycerin 5 mg/mL Injection USP 10 mL Single Dose Vial

Description

Rx Only

FOR INTRAVENOUS USE ONLY. NOT FOR DIRECT INTRAVENOUS INJECTION. NITROGLYCERIN INJECTION MUST BE DILUTED IN DEXTROSE (5%) INJECTION OR SODIUM CHLORIDE (0.9%) INJECTION PRIOR TO ITS INFUSION (SEE DOSAGE AND ADMINISTRATION SECTION). THE ADMINISTRATION SET USED FOR INFUSION WILL AFFECT THE AMOUNT OF NITROGLYCERIN INJECTION DELIVERED TO THE PATIENT. (SEE WARNINGS, AND DOSAGE AND ADMINISTRATION SECTIONS).

CAUTION
SEVERAL PREPARATIONS OF NITROGLYCERIN FOR INJECTION ARE AVAILABLE. THEY DIFFER IN CONCENTRATION AND/OR VOLUME PER VIAL. WHEN SWITCHING FROM ONE PRODUCT TO ANOTHER, ATTENTION MUST BE PAID TO THE DILUTION AND DOSAGE AND ADMINISTRATION INSTRUCTIONS.

DESCRIPTION:
Nitroglycerin is 1,2,3-propanetriol trinitrate, an organic nitrate whose structural formula is:

whose empiric formula is C3H5N3O9, and whose molecular weight is 227.09. The organic nitrates are vasodilators, active on both arteries and veins.
Nitroglycerin Injection, USP is a clear, practically colorless additive solution for intravenous infusion after dilution. Each mL contains: Nitroglycerin 5 mg, Alcohol 30% (v/v), Propylene Glycol 30%, and Water for Injection q.s. pH (range 3.0 to 6.5) may have been adjusted with Sodium Hydroxide and/or Hydrochloric Acid.
The solution is sterile, non-pyrogenic, and nonexplosive.

Clinical Pharmacology

The principal pharmacological action of Nitroglycerin Injection is relaxation of vascular smooth muscle and consequent dilatation of peripheral arteries and veins, especially the latter. Dilatation of the veins promotes peripheral pooling of blood and decreases venous return to the heart, thereby reducing left ventricular end-diastolic pressure and pulmonary capillary wedge pressure (preload). Arteriolar relaxation reduces systemic vascular resistance, systolic arterial pressure, and mean arterial pressure (afterload). Dilatation of the coronary arteries also occurs. The relative importance of preload reduction, afterload reduction, and coronary dilatation remains undefined. Dosing regimens for most chronically used drugs are designed to provide plasma concentrations that are continuously greater than a minimally effective concentration. This strategy is inappropriate for organic nitrates. Several well-controlled clinical trials have used exercise testing to assess the anti-anginal efficacy of continuously-delivered nitrates. In the large majority of these trials, active agents were indistinguishable from placebo after 24 hours (or less) of continuous therapy. Attempts to overcome nitrate tolerance by dose escalation, even to doses far in excess of those used acutely, have consistently failed. Only after nitrates have been absent from the body for several hours has their anti-anginal efficacy been restored.

Pharmacokinetics: The volume of distribution of nitroglycerin is about 3 L/kg, and nitroglycerin is cleared from this volume at extremely rapid rates, with a resulting serum half-life of about 3 minutes. The observed clearance rates (close to 1 L/kg/min) greatly exceed hepatic blood flow; known sites of extrahepatic metabolism include red blood cells and vascular walls.
The first products in the metabolism of nitroglycerin are inorganic nitrate and the 1,2- and 1,3- dinitroglycerols. The dinitrates are less effective vasodilators than nitroglycerin, but they are longer-lived in the serum, and their net contribution to the overall effect of chronic nitroglycerin regimens is not known. The dinitrates are further metabolized to (non-vasoactive) mononitrates and, ultimately, to glycerol and carbon dioxide.
To avoid development of tolerance to nitroglycerin, drug-free intervals of 10-12 hours are known to be sufficient; shorter intervals have not been well studied. In one well-controlled clinical trial, subjects receiving nitroglycerin appeared to exhibit a rebound or withdrawal effect, so that their exercise tolerance at the end of the daily drug-free interval was less than that exhibited by the parallel group receiving placebo.

Clinical Trials: Blinded, placebo-controlled trials of intravenous nitroglycerin have not been reported, but multiple investigators have reported open-label studies, and there are scattered reports of studies in which intravenous nitroglycerin was tested in blinded fashion against sodium nitroprusside. In each of these studies, therapeutic doses of intravenous nitroglycerin were found to reduce systolic and diastolic arterial blood pressure. The heart rate was usually increased, presumably as a reflexive response to the fall in blood pressure. Coronary perfusion
pressure was usually, but not always, maintained. Intravenous nitroglycerin reduced central venous pressure (CVP), right atrial pressure (RAP), pulmonary arterial pressure (PAP),
pulmonary-capillary wedge pressure (PCWP), pulmonary vascular resistance (PVR), and systemic vascular resistance (SVR). When these parameters were elevated, reducing them toward normal usually caused a rise in cardiac output. Conversely, intravenous nitroglycerin usually reduced cardiac output when it was given to patients whose CVP, RAP, PAP, PCWP, PVR, AND SVR were all normal. Most clinical trials of intravenous nitroglycerin have been brief; they have typically followed hemodynamic parameters during a single surgical procedure. In one careful study, one of the few that lasted more than a few hours, continuous intravenous nitroglycerin had lost almost all of its hemodynamic effect after 48 hours. In the same study, patients who received nitroglycerin infusions for only 12 hours out of each 24 demonstrated no similar attenuation of effect. These results are consistent with those seen in multiple large, double-blind, placebo-controlled trials of other formulations of nitroglycerin and other nitrates.

Indications and Usage

Nitroglycerin Injection is indicated for treatment of peri-operative hypertension; for control of congestive heart failure in the setting of acute myocardial infarction;for treatment of angina pectoris in patients who have not responded to sublingual nitroglycerin and b-blockers; and for induction of intraoperative hypotension.

Contraindications

Allergic reactions to organic nitrates are extremely rare, but they do occur. Nitroglycerin Injection is contraindicated in patients who are allergic to it.
In patients with pericardial tamponade, restrictive cardiomyopathy, or constrictive pericarditis, cardiac output is dependent upon venous return. Intravenous nitroglycerin is contraindicated in patients with these conditions.

Warnings

Amplification of the vasodilatory effects of nitroglycerin by sildenafil can result in severe hypotension. The time course and dose dependence of this interaction have not been studied. Appropriate supportive care has not been studied, but it seems reasonable to treat this as a nitrate overdose, with elevation of the extremities and with volume expansion.

Nitroglycerin readily migrates into many plastics, including the polyvinyl chloride (PVC) plastics commonly used for intravenous administration sets. Nitroglycerin absorption by PVC tubing is increased when the tubing is long, the flow rates are low, and the nitroglycerin concentration of the solution is high. The delivered fraction of the solution's original nitroglycerin content has been 20-60% in published studies using PVC tubing; the fraction varies with time during a single infusion, and no simple correction factor can be used. PVC tubing has been used in most published studies of intravenous nitroglycerin, but the reported doses have been calculated by simply multiplying the flow rate of the solution by the solution's original concentration of nitroglycerin. The actual doses delivered have been less, sometimes much less, than those reported. Some in-line intravenous filters also absorb nitroglycerin; these filters should be avoided.

Because of the problem of nitroglycerin absorption by polyvinyl chloride (PVC) tubing, Nitroglycerin Injection should be used with the least absorptive infusion tubing (i.e., non-PVC tubing) available.

DOSING INSTRUCTIONS MUST BE FOLLOWED WITH CARE. WHEN THE APPROPRIATE INFUSION SETS ARE USED, THE CALCULATED DOSE WILL BE DELIVERED TO THE PATIENT, BECAUSE THE LOSS OF NITROGLYCERIN INJECTION SEEN WITH STANDARD PVC TUBING WILL BE AVOIDED. THE DOSAGES REPORTED IN PUBLISHED STUDIES UTILIZED GENERAL-USE PVC ADMINISTRATION SETS, AND RECOMMENDED DOSES BASED ON THIS EXPERIENCE WILL BE TOO HIGH WHEN THE LOW-ABSORBING INFUSION SETS ARE USED.

Precautions

General: Severe hypotension and shock may occur with even small doses of nitroglycerin. This drug should therefore be used with caution in patients who may be volume depleted or who, for whatever reason, are already hypotensive. Hypotension induced by nitroglycerin may be accompanied by paradoxical bradycardia and increased angina pectoris. Nitrate therapy may aggravate the angina caused by hypertrophic cardiomyopathy. As tolerance to other forms of nitroglycerin develops, the effect of sublingual nitroglycerin on exercise tolerance, although still observable, is somewhat blunted. In industrial workers who have had long-term exposure to unknown (presumably high) doses of organic nitrates, tolerance clearly
occurs. Chest pain, acute myocardial infarction, and even sudden death have occurred during temporary withdrawal of nitrates from these workers, demonstrating the existence of true physical dependence. Some clinical trials in angina patients have provided nitroglycerin for about 12 continuous hours of every 24- hour day. During the nitrate-free intervals in some of these trials, anginal attacks have been more easily provoked than before treatment, and patients have demonstrated hemodynamic rebound and decreased exercise tolerance. The importance of these observations to the routine, clinical use of intravenous nitroglycerin is not known. Lower concentrations of nitroglycerin increase the potential precision of dosing, but these concentrations increase the total fluid volume that must be delivered to the patient. Total fluid load may be a dominant consideration in patients with compromised function of the heart, liver, and/or kidneys. Nitroglycerin infusions should be administered only via a pump that can maintain a constant infusion rate. Intracoronary injection of nitroglycerin infusions has not been studied.
Laboratory Tests: Because of the propylene glycol content of intravenous nitroglycerin, serum triglyceride assays that rely on glycerol oxidase may give falsely elevated results in patients receiving this medication.
Drug Interactions: The vasodilating effects of nitroglycerin may be additive with those of other vasodilators. Administration of nitroglycerin infusions through the same infusion set as blood can result in pseudoagglutination and hemolysis. More generally, nitroglycerin in 5% dextrose or sodium chloride 0.9% should not be mixed with any other medication of any kind.
Intravenous nitroglycerin interferes, at least in some patients, with the anticoagulant effect of heparin. In patients receiving intravenous nitroglycerin, concomitant heparin therapy should be guided by frequent measurement of the activated partial thromboplastin time.
Carcinogenesis, Mutagenesis, Impairment of Fertility: Animal carcinogenesis studies with injectable nitroglycerin have not been performed.
Rats receiving up to 434 mg/kg/day of dietary nitroglycerin for 2 years developed dose-related fibrotic and neoplastic changes in liver, including carcinomas, and interstitial cell tumors in testes. At high dose, the incidences of hepatocellular carcinomas in both sexes were 52% vs. 0% in controls, and incidences of testicular tumors were 52% vs. 8% in controls. Lifetime dietary administration of up to 1058 mg/kg/day of nitroglycerin was not tumorigenic in mice. Nitroglycerin was weakly mutagenic in Ames tests performed in two different laboratories. There was no evidence of mutagenicity in an in vivo dominant lethal assay with male rats treated with doses up to about 363 mg/kg/day, p.o., or in in vitro cytogenetic tests in rat and dog tissues. In a three-generation reproduction study, rats received dietary nitroglycerin at doses up to about 434 mg/kg/day for six months prior to mating of the F0 generation with treatment continuing through successive F1 and F2 generations. The high-dose was associated with decreased feed intake and body weight gain in both sexes at all matings. No specific effect on the fertility of the F0 generation was seen. Infertility noted in subsequent generations, however, was attributed to increased interstitial cell tissue and aspermatogenesis in the high dose males. In this three-generation study there was no clear evidence of teratogenicity.
Pregnancy: Pregnancy Category C: Animal teratology studies have not been conducted with nitroglycerin injection. Teratology studies in rats and rabbits, however, were conducted with topically applied nitroglycerin ointment at doses up to 80 mg/kg/day and 240 mg/kg/day, respectively. No toxic effects on dams or fetuses were seen at any dose tested. There are no adequate and wellcontrolled studies in pregnant women. Nitroglycerin should be given to a pregnant woman only if clearly needed.
Nursing Mothers: It is not known whether nitroglycerin is excreted in human milk. Because many drugs are excreted in human milk, caution should be exercised when nitroglycerin is administered to a nursing woman.
Pediatric Use: Safety and effectiveness in children have not been established.

Adverse Reactions

Adverse reactions to nitroglycerin are generally dose-related and almost all of these reactions are the result of nitroglycerin's activity as a vasodilator. Headache, which may be severe, is the most commonly reported side effect. Headache may be recurrent with each daily dose, especially at higher doses. Transient episodes of lightheadedness, occasionally related to blood pressure changes, may also occur. Hypotension occurs infrequently, but in some patients it may be severe enough to warrant discontinuation of therapy. Syncope, crescendo angina, and rebound hypertension have been reported but are uncommon. Extremely rarely, ordinary doses of organic nitrates have caused methemoglobinemia in normal-seeming patients. Methemoglobinemia is so infrequent at these doses that further discussion of its diagnosis and treatment is deferred (see OVERDOSAGE).

Overdosage

Hemodynamic Effects: The ill effects of nitroglycerin overdose are generally the results of nitroglycerin's capacity to induce vasodilatation, venous pooling, reduced cardiac output, and hypotension. These hemodynamic changes may have protean manifestations, including increased intracranial pressure, with any or all of persistent throbbing headache, confusion, and moderate fever; vertigo; palpitation; visual disturbances; nausea and vomiting (possibly with colic and even bloody diarrhea); syncope (especially in the upright posture); air hunger and dyspnea, later followed by reduced ventilatory effort; diaphoresis, with the skin either flushed or cold and clammy; heart block and bradycardia; paralysis; coma; seizures; and death.
Laboratory determinations of serum levels of nitroglycerin and its metabolites are not widely available, and such determinations have, in any event, no established role in the management of nitroglycerin overdose. No data are available to suggest physiological maneuvers (e.g., maneuvers to change the pH of the urine) that might accelerate elimination of nitroglycerin and its active metabolites. Similarly, it is not known which- if any-of these substances can usefully be removed from the body by hemodialysis. No specific antagonist to the vasodilator effects of nitroglycerin is known, and no intervention has been subject to controlled study as a therapy of nitroglycerin overdose. Because the hypotension associated with nitroglycerin overdose is the result of venodilatation and arterial hypovolemia, prudent therapy in this situation should be directed toward increase in central fluid volume. Passive elevation of the patient's legs may be sufficient, but intravenous infusion of normal saline or similar fluid may also be necessary. The use of epinephrine or other arterial vasoconstrictors in this setting is likely to do more harm than good. In patients with renal disease or congestive heart failure, therapy resulting in central volume expansion is not without hazard. Treatment of nitroglycerin overdose in these patients may be subtle and difficult, and invasive monitoring may be required.
Methemoglobinemia: Nitrate ions liberated during metabolism of nitroglycerin can oxidize hemoglobin into methemoglobin. Even in patients totally without cytochrome b5 reductase activity, however, and even assuming that the nitrate moieties of nitroglycerin are quantitatively applied to oxidation of hemoglobin, about 1 mg/kg of nitroglycerin should be required before any of these patients manifests clinically significant (³10%) methemoglobinemia. In patients with normal reductase function, significant production of methemoglobin should require even larger doses of nitroglycerin. In one study in which 36 patients received 2-4 weeks of continuous nitroglycerin therapy at 3.1 to 4.4 mg/hr, the average methemoglobin level measured was 0.2%; this was comparable to that observed in parallel patients who received placebo. Notwithstanding these observations, there are case reports of significant methemoglobinemia in association with moderate overdoses of organic nitrates. None of the affected patients had been thought to be unusually susceptible. Methemoglobin levels are available from most clinical laboratories. The diagnosis should be suspected in patients who exhibit signs of impaired oxygen delivery despite adequate cardiac output and adequate arterial pO2. Classically, methemoglobinemic blood is
described as chocolate brown, without color change on exposure to air. When methemoglobinemia is diagnosed, the treatment of choice is methylene blue, 1-2 mg/kg intravenously.

Dosage and Administration

NOT FOR DIRECT INTRAVENOUS INJECTION
NITROGLYCERIN INJECTION IS A CONCENTRATED, POTENT DRUG WHICH MUST BE DILUTED IN DEXTROSE (5%) INJECTION OR SODIUM CHLORIDE (0.9%) INJECTION PRIOR TO ITS INFUSION. NITROGLYCERIN INJECTION SHOULD NOT BE MIXED WITH OTHER DRUGS.

1. Initial Dilution:

Aseptically transfer the contents of one nitroglycerin vial (containing 25 mg or 50 mg of nitroglycerin) into a 500 mL glass bottle of either Dextrose (5%) Injection or Sodium Chloride Injection (0.9%). This yields a final concentration of 50 mcg/mL or 100 mcg/mL. Diluting 5 mg nitroglycerin into 100 mL will also yield a final concentration of 50 mcg/mL.

2. Maintenance Dilution:

It is important to consider the fluid requirements of the patient as well as the expected duration of infusion in selecting the appropriate dilution of Nitroglycerin Injection.
After the initial dosage titration, the concentration of the solution may be increased, if necessary, to limit fluids given to the patient. The nitroglycerin concentration should not exceed 400 mcg/mL. See chart.

Note: If the concentration is adjusted, it is imperative to flush or replace the infusion set before a new concentration is utilized. If the set were not flushed or replaced, it could take minutes to hours, depending upon the flow rate and the dead space of the set, for the new concentration to reach the patient. Invert the glass parenteral bottle several times to assure uniform dilution of the nitroglycerin. Dosage is affected by the type of container and administration set used. See WARNINGS. Although the usual starting adult dose range reported in clinical studies was 25 mcg/min or more, these studies used PVC administration sets. THE USE OF NON-ABSORBING TUBING WILL RESULT IN THE NEED FOR REDUCED DOSES. If a peristaltic action infusion pump is used, an appropriate administration set should be selected with a drip chamber that delivers approximately 60 microdrops/mL. Table 1 and the Nitroglycerin Injection Dilution Table below may be used to calculate the nitroglycerin dilution and flow rate in microdrops/minute to achieve the desired Nitroglycerin Injection administration rate. If a volumetric infusion pump is used, an appropriate volumetric infusion pump connector set should be selected. Table 1 below may still be used; however, flow rate will be determined directly by the infusion pump, independent of the drop size of the appropriate set drip chambers. Thus, the reference to ``microdrops/min## is not applicable, and the corresponding flow rate in mL/hr should be used to determine pump settings. When using a non-absorbing infusion set, the initial dosage should be 5 mcg/min delivered through an infusion pump capable of exact
and constant delivery of the drug. Subsequent titration must be adjusted to the clinical situation, with dose increments becoming more cautious as partial response is seen. Initial titration should be in 5 mcg/min increments, with increases every 3-5 minutes until some response is noted. If no response is seen at 20 mcg/min, increments of 10 and later 20 mcg/min can be used. Once a partial blood pressure response is observed, the dose increase should be reduced and the interval between increases should be lengthened. Some patients with normal or low left ventricular filling pressures or pulmonary capillary wedge pressure (e.g., angina patients without other complications) may be hypersensitive to the effects of nitroglycerin and may respond fully to doses as small as 5 mcg/ min. These patients require especially careful titration and monitoring. There is no fixed optimum dose of nitroglycerin. Due to variations in the responsiveness of individual patients to the drug, each patient must be titrated to the desired level of hemodynamic function. Therefore, continuous monitoring of physiologic parameters (i.e., blood pressure and heart rate in all patients, other measurements such as pulmonary capillary wedge pressure, as appropriate) MUST be performed to achieve the correct dose. Adequate systemic blood pressure and coronary perfusion pressure must be maintained.

Dilution:
Nitroglycerin Injection is supplied in 5 mg/mL solution. A dilution and administration scheme for Nitroglycerin Injection is shown in Table 1 below.

60 MICRODROPS=1mL

Solution Concentration (mcg/mL) | 100 | 200 | 400
Dose (mcg/min) | FLOW RATE (microdrops/min=mL/hr
5 | 3 | - | -
10 | 6 | 3 | -
15 | 9 | - | -
20 | 12 | 6 | 3
30 | 18 | 9 | -
40 | 24 | 12 | 6
60 | 36 | 18 | 9
80 | 48 | 24 | 12
120 | 72 | 36 | 18
160 | 96 | 48 | 24
240 | - | 72 | 36
320 | - | 96 | 48
480 | - | - | 72
640 | - | - | 96

60MICRODROPS=1 mL

NITROGLYCERIN INJECTION DILUTION TABLE

Each mL of Nitroglycerin Injection contains 5 mg of nitroglycerin.

Total Contents: Each 10 mL vial contains 50 mg of nitroglycerin.

FINAL CONCENTRATION

mL of Nitroglycerin Injection Volume | mg | 100 mcg/mL q.s. to | 200 mcg/mL q.s. to | 400 mcg/mL q.s. to
5 mL | 25 mg | 250 mL | 125 mL | ---
10 mL | 50 mg | 500 mL | 250 mL | 125 mL
20 mL | 100 mg | 1000 mL | 500 mL | 250 mL
40 mL | 200 mg | --- | 1000 mL | 500 mL

(Diluent: Dectrose 5% Injection of Sodium Chloride Injection (0.9%)

NOTE: Parenteral drug products should be inspected visually for particulate matter and discoloration prior to administration whenever solution and container permit.

How Supplied

Nitroglycerin Injection, USP, 5mg/mL is available as follows:
NDC 0517-4810-25 50mg/10 mL Single Dose Vial Package of 25
PROTECT FROM LIGHT. RETAIN IN CARTON UNTIL TIME OF USE.
Store at 20°-25°C (68°-77°F); excursions permitted to 15° to 30°C (59° to 86°F) (See USP Controlled Room Temperature).
DISCARD UNUSED PORTION.

Product repackaged by: Henry Schein, Inc., Bastian, VA 24314
From Original Manufacturer/Distributor's NDC and Unit of Sale | To Henry Schein Repackaged Product NDC and Unit of Sale | Total Strength/Total Volume (Concentration) per unit
NDC 0517-4810-25 Packages of 25 | NDC 0404-9928-10 1 10 mL Single Dose Vial in a bag (Vial bears NDC 0517-4810-01) | 50 mg/10 mL

AMERICAN
REGENT
LABORATORIES, INC.
SHIRLEY, NY 11967
IN4805
Rev. 11/05